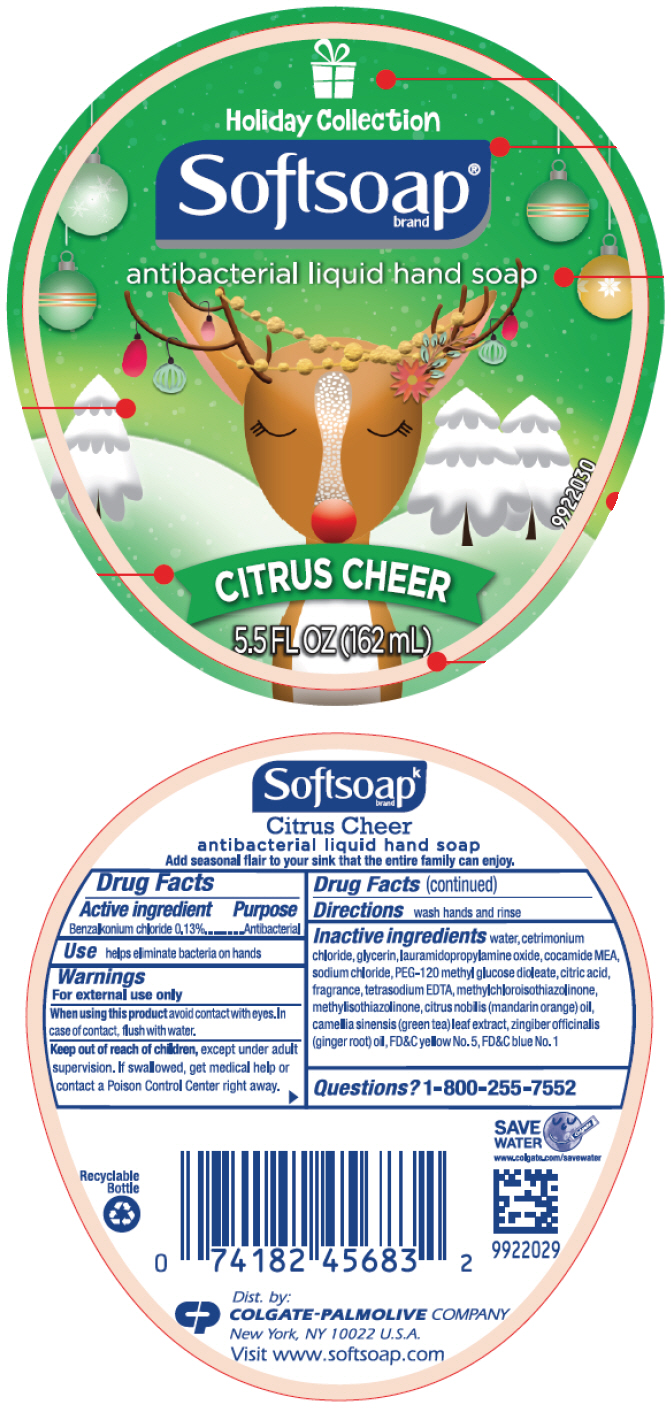 DRUG LABEL: SoftSoap Antibacterial Hand Citrus Cheer
NDC: 35000-733 | Form: LIQUID
Manufacturer: COLGATE PALMOLIVE COMPANY
Category: otc | Type: HUMAN OTC DRUG LABEL
Date: 20191211

ACTIVE INGREDIENTS: BENZALKONIUM CHLORIDE 1.33 mg/1 mL
INACTIVE INGREDIENTS: WATER; CETRIMONIUM CHLORIDE; GLYCERIN; LAURAMIDOPROPYLAMINE OXIDE; COCO MONOETHANOLAMIDE; SODIUM CHLORIDE; PEG-120 METHYL GLUCOSE DIOLEATE; CITRIC ACID MONOHYDRATE; EDETATE SODIUM; METHYLCHLOROISOTHIAZOLINONE; METHYLISOTHIAZOLINONE; MANDARIN OIL; GREEN TEA LEAF; GINGER OIL; FD&C YELLOW NO. 5; FD&C BLUE NO. 1

SoftSoap® Antibacterial Hand Soap Citrus Cheer (162 ml)

Drug Facts

Active ingredient

Benzalkonium chloride 0.13%

Purpose

Antibacterial

Use

helps eliminate bacteria on hands

Warnings

For external use only

When using this product avoid contact with eyes. In case of contact, flush with water.

Keep out of reach of children, except under adult supervision. If swallowed, get medical help or contact a Poison Control Center right away.

Directions

wash hands and rinse

Inactive ingredients

water, cetrimonium chloride, glycerin, lauramidopropylamine oxide, cocamide MEA, sodium chloride, PEG-120 methyl glucose dioleate, citric acid, fragrance, tetrasodium EDTA, methylchloroisothiazolinone, methylisothiazolinone, citrus nobilis (mandarin orange) oil, camellia sinensis (green tea) leaf extract, zingiber officinalis (ginger root) oil, FD&C yellow No. 5, FD&C blue No. 1

Questions?

1-800-255-7552

Dist. by:
COLGATE-PALMOLIVE COMPANY
New York, NY 10022 U.S.A.

PRINCIPAL DISPLAY PANEL - 162 mL Bottle Label

Holiday Collection

Softsoap®
brand

antibacterial liquid hand soap

CITRUS CHEER

5.5 FL OZ (162 ml)

9922030